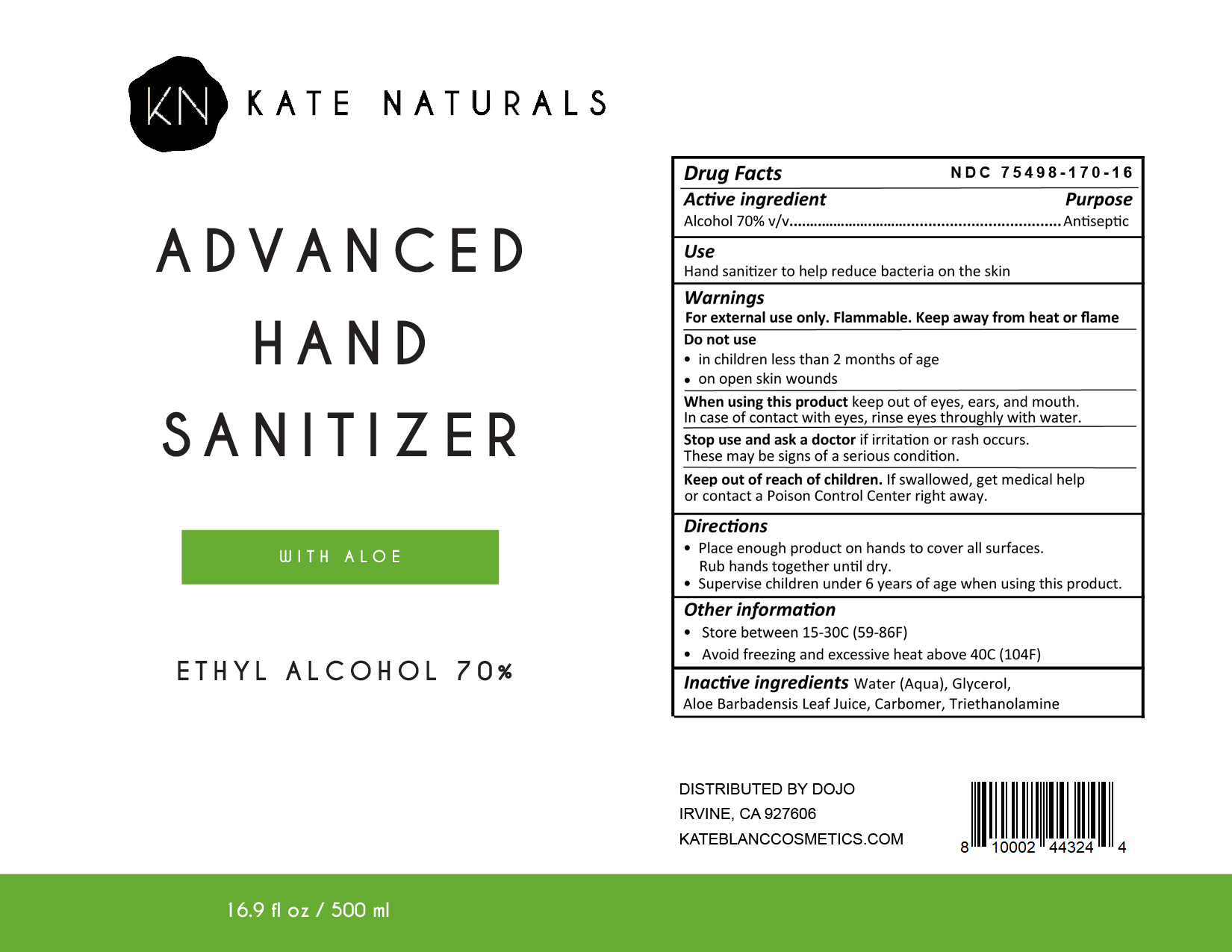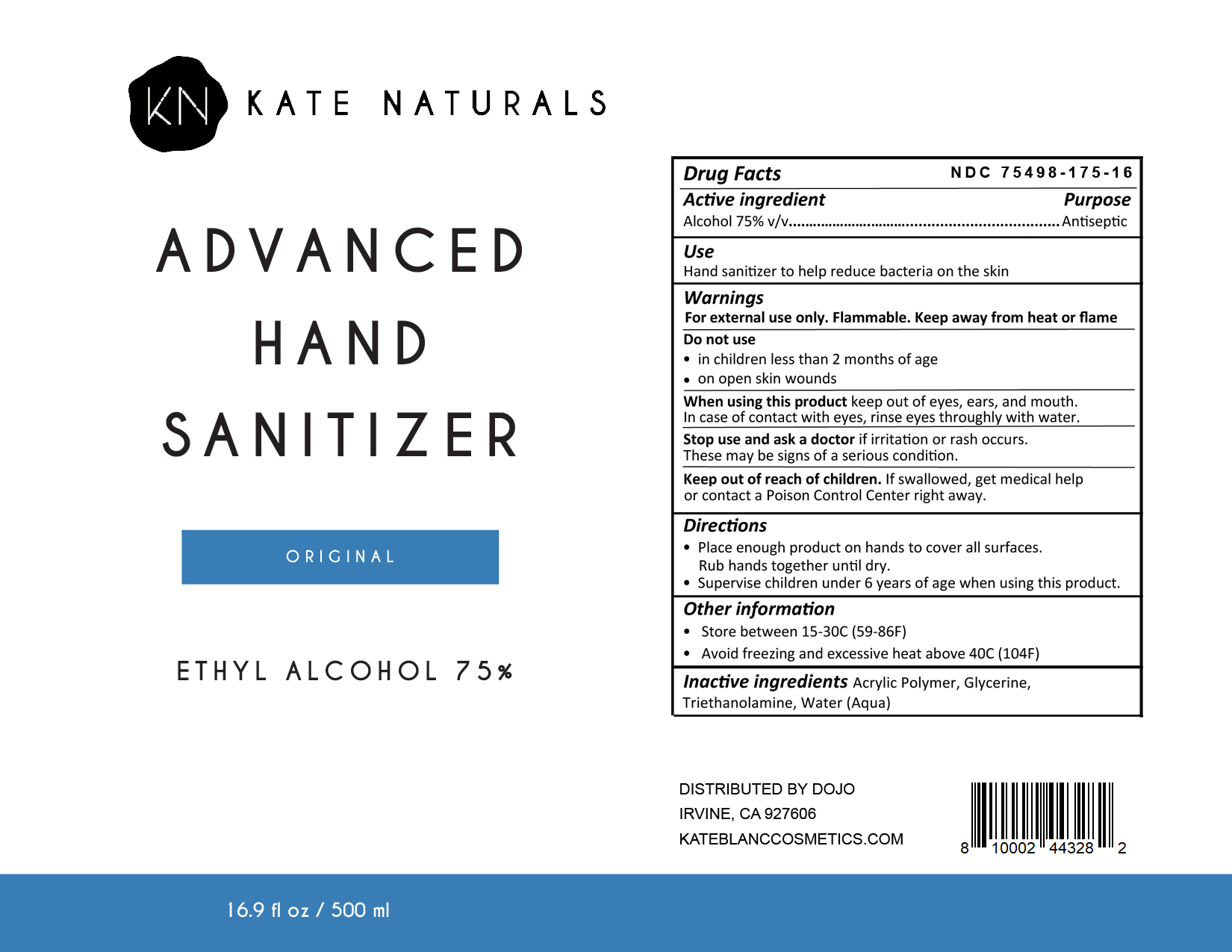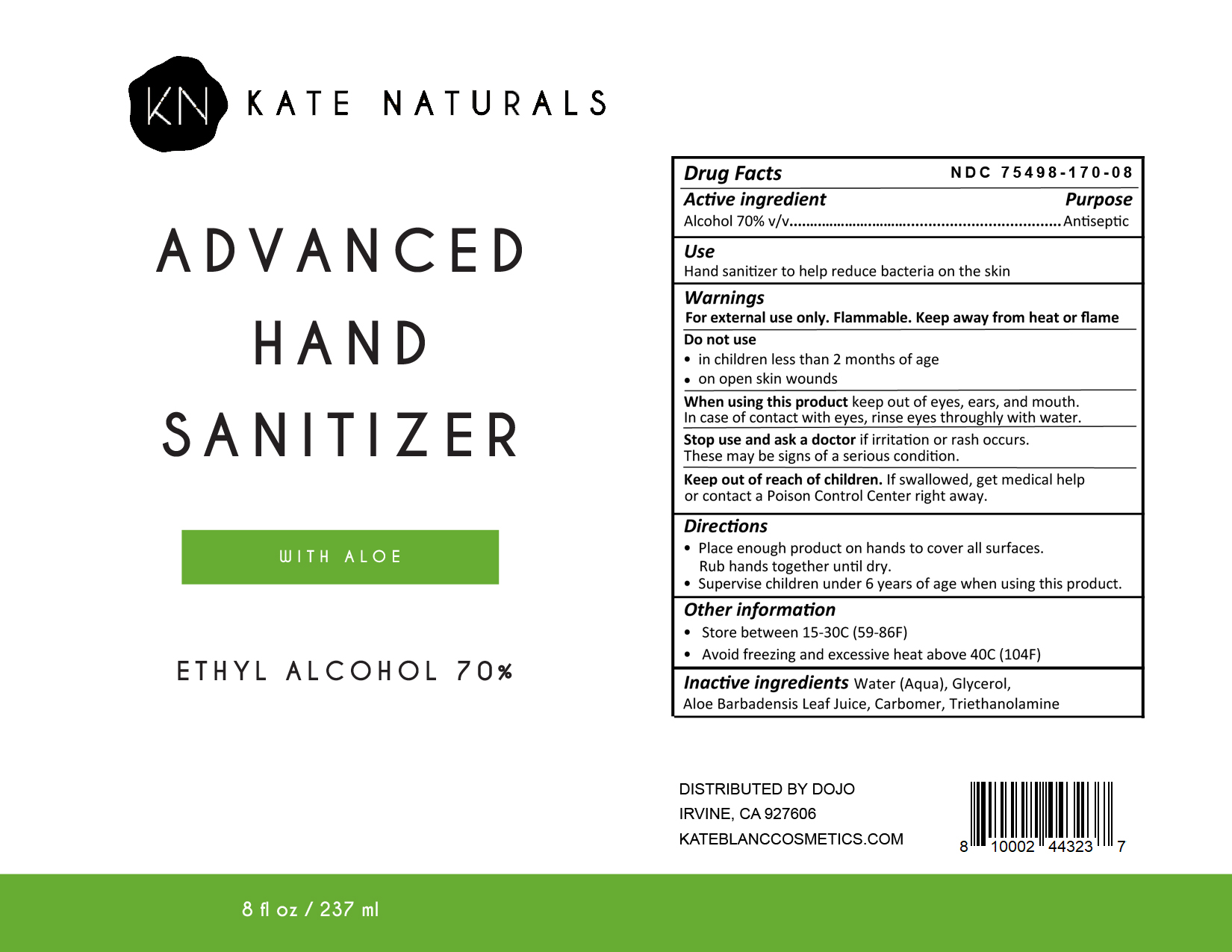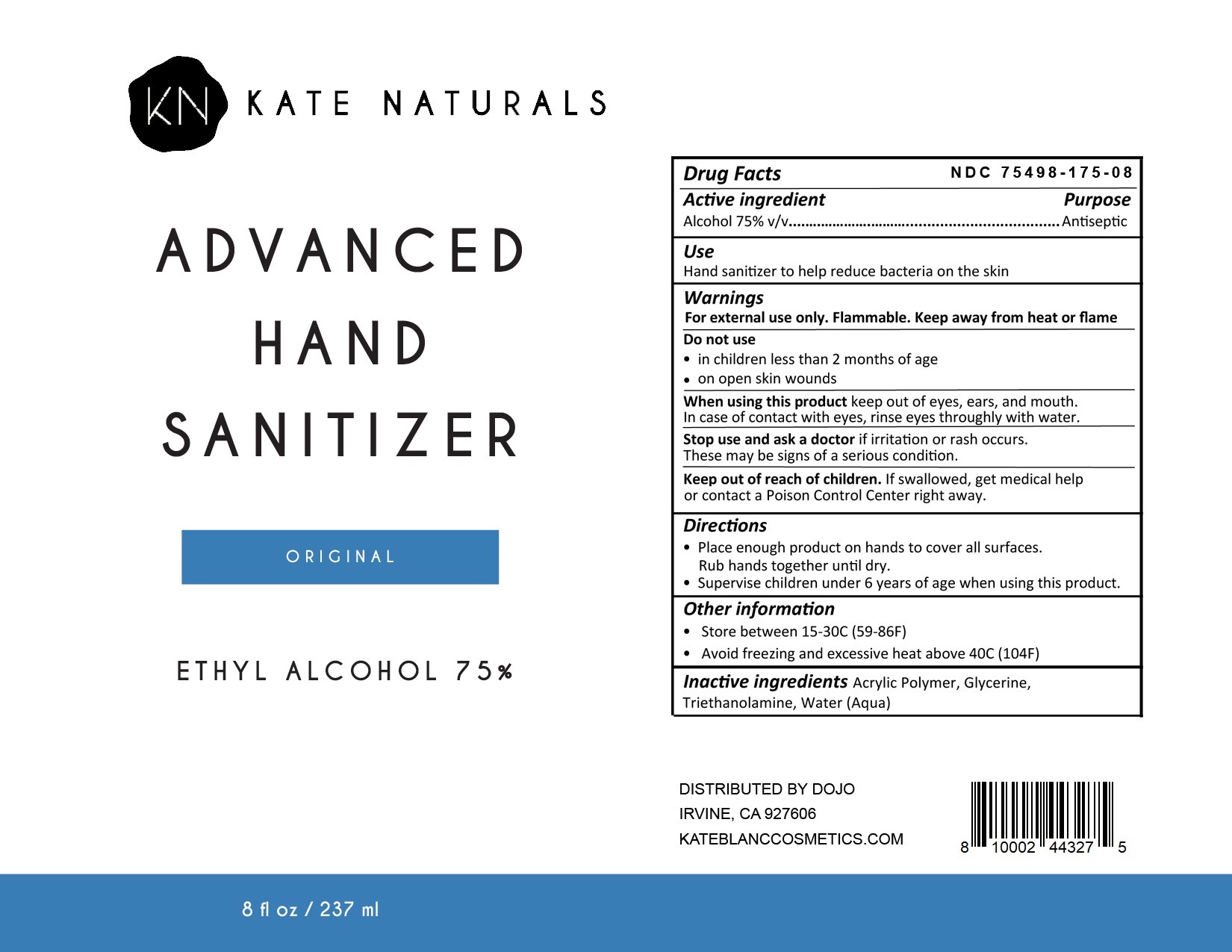 DRUG LABEL: Kate Naturals Advanced Hand Sanitizer Original
NDC: 75498-175 | Form: GEL
Manufacturer: THE DOJO LLC
Category: otc | Type: HUMAN OTC DRUG LABEL
Date: 20200509

ACTIVE INGREDIENTS: ALCOHOL 75 mL/100 mL
INACTIVE INGREDIENTS: ACRYLIC ACID/SODIUM ACRYLATE COPOLYMER (1:1; 600 MPA.S AT 0.2%); GLYCERIN; TROLAMINE; WATER

This hand sanitizer is manufactured using the following ingredients:

Ethyl Alcohol (70%, v/v) in an aqueous solution denatured according to Alcohol and Tobacco Tax and Trade Bureau regulations in 27 CFR part 20.

Aloe Barbadensis Leaf

Carbomer

Glycerol

Triethanolamine

Active Ingredients(s)

Ethyl Alcohol 70% v/v. Purpose: Antiseptic

Purpose

Antiseptic, Hand Sanitizer

Use

Hand sanitizer to help reduce bacteria on the skin

Warnings

For external use only. Flammable. Keep away from heat or flame

When using this product, keep out of eyes, ears, and mouth.

In case of contact with eyes, rinse eyes throughly with water.

Stop use and ask a doctor if irritation or rash occurs. These may be signs of a serious condition.

Keep out of reach of children. If swallowed, get medical help or contact a Poison Control Center right away.

Directions

- Place enough product on hands to cover all surfaces. Rub hands together until dry.
- Supervise children under 6 years of age when using this product.

Other information

Store under 105F

Inactive ingredients

Water (Aqua), Glycerol, Aloe Barbadensis Leaf Juice, Carbomer, Triethanolamine

Package Level - Principal Display Panel

500ml NDC: 75498-170-16

Package Label - Principal Display Panel

237ml NDC: 75498-170-08

Package Label - Principal Display Panel

237ml NDC: 75498-175-08

Package Label - Principala Display Panel

500ml NDC: 75498-175-16